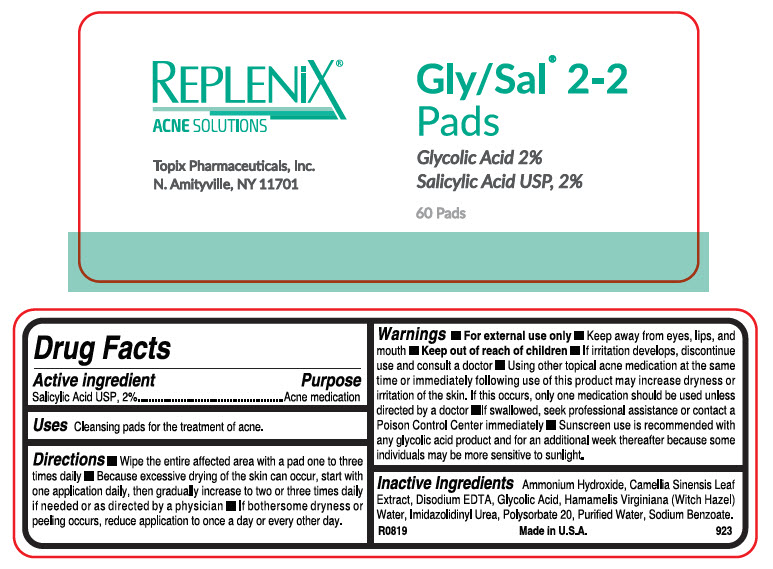 DRUG LABEL: Gly-Sal 2-2 Pads
NDC: 51326-923 | Form: CLOTH
Manufacturer: Topiderm, Inc.
Category: otc | Type: HUMAN OTC DRUG LABEL
Date: 20230216

ACTIVE INGREDIENTS: SALICYLIC ACID 20 mg/1 1
INACTIVE INGREDIENTS: AMMONIA; GREEN TEA LEAF; EDETATE DISODIUM; GLYCOLIC ACID; HAMAMELIS VIRGINIANA TOP WATER; IMIDUREA; POLYSORBATE 20; WATER; SODIUM BENZOATE; ZINC PIDOLATE

Gly-Sal® 2-2 Pads

Drug Facts

Active ingredient

Salicylic Acid USP, 2%

Purpose

Acne medication

Uses

Cleansing pads for the treatment of acne.

Directions

- Wipe the entire affected area with a pad one to three times daily
- Because excessive drying of the skin can occur, start with one application daily, then gradually increase to two or three times daily if needed or as directed by a physician
- If bothersome dryness or peeling occurs, reduce application to once a day or every other day.

Warnings

- For external use only
- Keep away from eyes, lips, and mouth

- Keep out of reach of children
- If irritation develops, discontinue use and consult a doctor
- Using other topical acne medication at the same time or immediately following use of this product may increase dryness or irritation of the skin. If this occurs, only one medication should be used unless directed by a doctor
- If swallowed, seek professional assistance or contact a Poison Control Center immediately
- Sunscreen use is recommended with any glycolic acid product and for an additional week thereafter because some individuals may be more sensitive to sunlight.

Inactive Ingredients

Ammonium Hydroxide, Camellia Sinensis Leaf Extract, Disodium EDTA, Glycolic Acid, Hamamelis Virginiana (Witch Hazel) Water, Imidazolidinyl Urea, Polysorbate 20, Purified Water, Sodium Benzoate.

PRINCIPAL DISPLAY PANEL - 60 Pad Jar Label

REPLENiX®
ACNE SOLUTIONS

Topix Pharmaceuticals, Inc.
N. Amityville, NY 11701

Gly/Sal® 2-2
Pads

Glycolic Acid 2%
Salicylic Acid USP, 2%

60 Pads